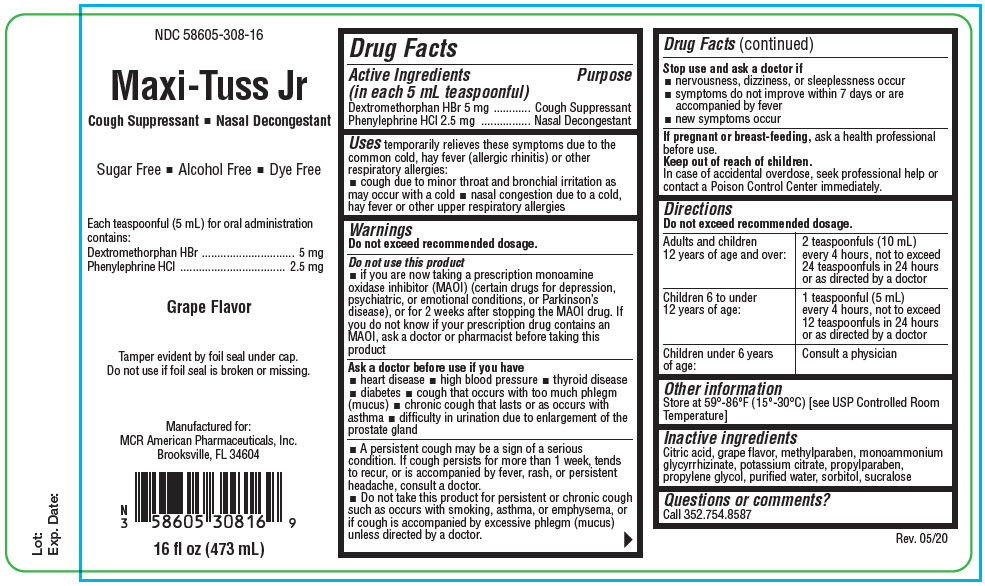 DRUG LABEL: Maxi-Tuss Jr
NDC: 58605-308 | Form: LIQUID
Manufacturer: MCR American Pharmaceuticals, Inc.
Category: otc | Type: HUMAN OTC DRUG LABEL
Date: 20200624

ACTIVE INGREDIENTS: Dextromethorphan Hydrobromide 5 mg/5 mL; Phenylephrine Hydrochloride 2.5 mg/5 mL
INACTIVE INGREDIENTS: CITRIC ACID MONOHYDRATE; Methylparaben; AMMONIUM GLYCYRRHIZATE; Potassium Citrate; Propylparaben; Propylene Glycol; WATER; Sorbitol; Sucralose

Maxi-Tuss Jr

Drug Facts

ACTIVE INGREDIENT

Active Ingredients (in each 5 mL teaspoonful) | Purpose
Dextromethorphan HBr 5 mg | Cough Suppressant
Phenylephrine HCl 2.5 mg | Nasal Decongestant

Uses

temporarily relieves these symptoms due to the common cold, hay fever (allergic rhinitis) or other respiratory allergies:

- cough due to minor throat and bronchial irritation as may occur with a cold
- nasal congestion due to a cold, hay fever or other upper respiratory allergies

Warnings

Do not exceed recommended dosage.

Do not use this product

- if you are now taking a prescription monoamine oxidase inhibitor (MAOI) (certain drugs for depression, psychiatric, or emotional conditions, or Parkinson's disease), or for 2 weeks after stopping the MAOI drug. If you do not know if your prescription drug contains an MAOI, ask a doctor or pharmacist before taking this product

Ask a doctor before use if you have

- heart disease
- high blood pressure
- thyroid disease
- diabetes
- cough that occurs with too much phlegm (mucus)
- chronic cough that lasts or as occurs with asthma
- difficulty in urination due to enlargement of the prostate gland

- A persistent cough may be a sign of a serious condition. If cough persists for more than 1 week, tends to recur, or is accompanied by fever, rash, or persistent headache, consult a doctor.
- Do not take this product for persistent or chronic cough such as occurs with smoking, asthma, or emphysema, or if cough is accompanied by excessive phlegm (mucus) unless directed by a doctor.

Stop use and ask a doctor if

- nervousness, dizziness, or sleeplessness occur
- symptoms do not improve within 7 days or are accompanied by fever
- new symptoms occur

PREGNANCY OR BREAST FEEDING

If pregnant or breast-feeding, ask a health professional before use.

Keep out of reach of children.

In case of accidental overdose, seek professional help or contact a Poison Control Center immediately.

Directions

Do not exceed recommended dosage.

Adults and children 12 years of age and over: | 2 teaspoonfuls (10 mL) every 4 hours, not to exceed 24 teaspoonfuls in 24 hours or as directed by a doctor
Children 6 to under 12 years of age: | 1 teaspoonful (5 mL) every 4 hours, not to exceed 12 teaspoonfuls in 24 hours or as directed by a doctor
Children under 6 years of age: | Consult a physician

Other information

Store at 59°-86°F (15°-30°C) [see USP Controlled Room Temperature]

Inactive ingredients

Citric acid, grape flavor, methylparaben, monoammonium glycyrrhizinate, potassium citrate, propylparaben, propylene glycol, purified water, sorbitol, sucralose

Questions or comments?

Call 352.754.8587

PRINCIPAL DISPLAY PANEL - 473 mL Bottle Label

NDC 58605-308-16

Maxi-Tuss Jr
Cough Suppressant ■ Nasal Decongestant

Sugar Free ■ Alcohol Free ■ Dye Free

Each teaspoonful (5 mL) for oral administration
contains:
Dextromethorphan HBr 5 mg
Phenylephrine HCl 2.5 mg

Grape Flavor

Tamper evident by foil seal under cap.
Do not use if foil seal is broken or missing.

Manufactured for:
MCR American Pharmaceuticals, Inc.
Brooksville, FL 34604

16 fl oz (473 mL)